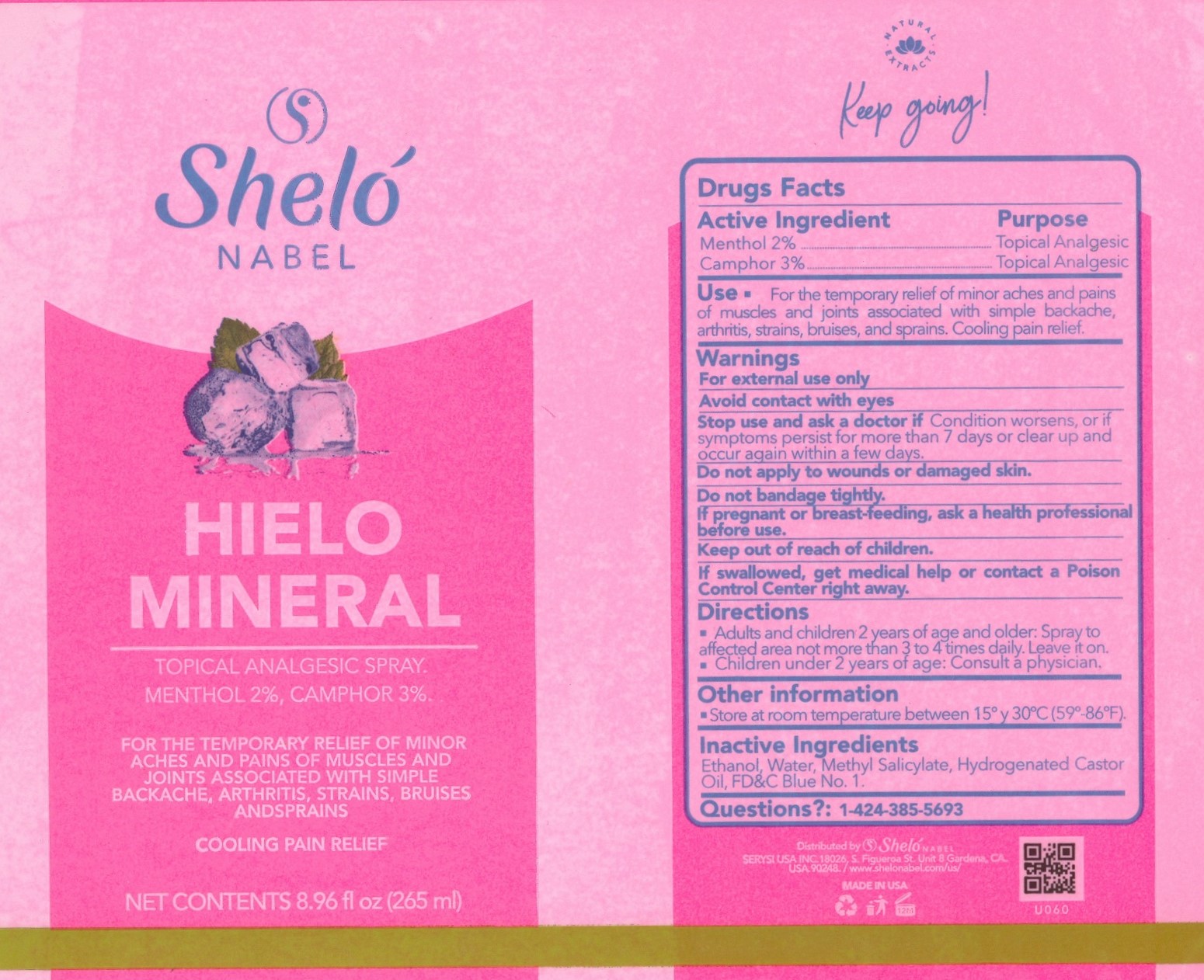 DRUG LABEL: Hielo Mineral
NDC: 65112-261 | Form: LIQUID
Manufacturer: I Shay Cosmetics Inc
Category: otc | Type: HUMAN OTC DRUG LABEL
Date: 20221018

ACTIVE INGREDIENTS: MENTHOL 0.02 g/1 g; CAMPHOR (SYNTHETIC) 0.03 g/1 g
INACTIVE INGREDIENTS: WATER 0.18 g/1 g; ALCOHOL 0.65 g/1 g

Topical Analgesic Spray

Active Ingredient

Menthol 2%..................... Topical Analgesic

Camphor 3%................... Topical Analgesic

PURPOSE

For the temporary relief of minor aches and pains of muscles and joints associated with simple backache, arthritis, strains, bruises, and sprains. Cooling pain relief.

WARNINGS - Keep out of reach of children

INDICATIONS AND USAGE

For the temporary relief of minor aches and pains of muscles and joints associated with simple backache, arthritis, strains, bruises, and sprains. Cooling pain relief.

Inactive Ingredients

Ethanol, Water, Methyl Salicylate, Hydrogenated Castor Oil, FD&C Blue No. 1.

Warnings

For external use only

Avoid contact with eyes

Stop use and ask a doctor if condition worsens or if symptoms persist for more than 7 days or clear up and occur again within a few days.

Do not apply to wounds or damaged skin

Do not bandage tightly

If pregnant or breast-feeding, ask a health professional before use

Keep out of reach of children

If swallowed, get medical help or contact a poison control center right away

DIRECTIONS

Adults ands children 2 years of age and older: Spray to affected area not more than 3 to 4 times daily. Leave it on.

Children under 2 years of age: Consult a physician

Other Information

Store at room temperature between 15°and 30°C (59°-86°F)